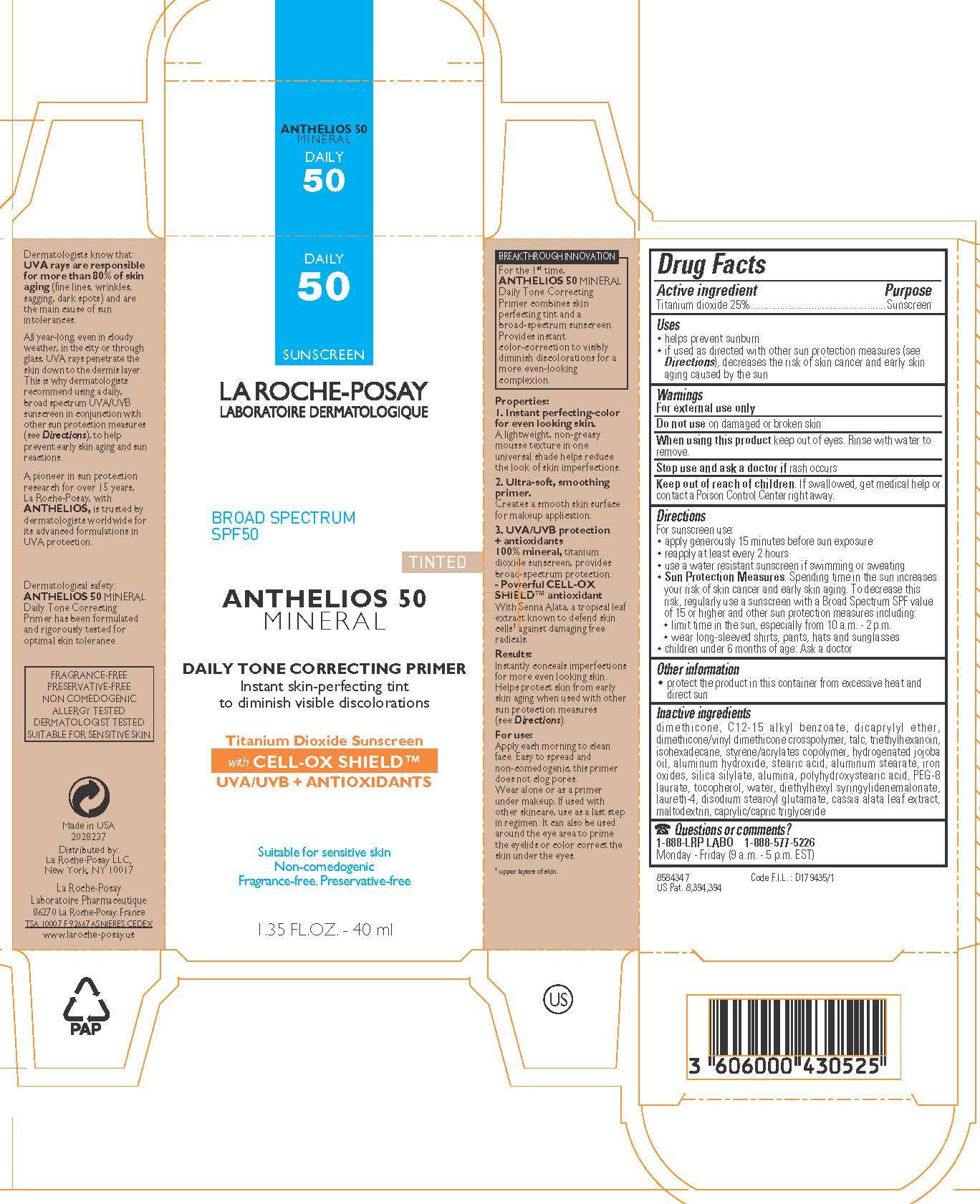 DRUG LABEL: La Roche Posay Laboratoire Dermatologique Anthelios 50 Mineral Daily Tone Correcting Primer Broad Spectrum SPF 50 Sunscreen
NDC: 49967-525 | Form: LOTION
Manufacturer: L'Oreal USA Products Inc
Category: otc | Type: HUMAN OTC DRUG LABEL
Date: 20240101

ACTIVE INGREDIENTS: TITANIUM DIOXIDE 250 mg/1 mL
INACTIVE INGREDIENTS: DIMETHICONE; ALKYL (C12-15) BENZOATE; DICAPRYLYL ETHER; DIMETHICONE/VINYL DIMETHICONE CROSSPOLYMER (HARD PARTICLE); TALC; TRIETHYLHEXANOIN; ISOHEXADECANE; STYRENE/ACRYLAMIDE COPOLYMER (500000 MW); HYDROGENATED JOJOBA OIL; ALUMINUM HYDROXIDE; STEARIC ACID; ALUMINUM STEARATE; FERRIC OXIDE RED; ALUMINUM OXIDE; POLYHYDROXYSTEARIC ACID (2300 MW); PEG-8 LAURATE; TOCOPHEROL; WATER; DIETHYLHEXYL SYRINGYLIDENEMALONATE; LAURETH-4; DISODIUM STEAROYL GLUTAMATE; SENNA ALATA LEAF; MALTODEXTRIN; MEDIUM-CHAIN TRIGLYCERIDES

Drug Facts

Active ingredient

Titanium dioxide 25%

Purpose

Sunscreen

Uses

- helps prevent sunburn
- if used as directed (see Directions), decreases the risk of skin cancer and early skin aging caused by the sun

Warnings

For external use only

Do not use

on damaged or broken skin

When using tjhis product

keep out of eyes. Rinse with water to remove.

Stop use and ask a doctor if

rash occurs

Keep out of reach of children.

If swallowed, get medical help or contact a Poison Control Center right away.

Directions

For sunscreen use:

- apply generously 15 minutes before sun exposure
- reapply at least every 2 hours
- use a water resistant sunscreen if swimming or sweating
- Sun Protection Measures. Spending time in the sun increases your risk of skin cancer and early skin aging. To decrease this risk regularly use a sunscreen with a Broad Spectrum SPF value of 15 of higher and other sun protection measures including:

- limit time in the sun, especially from 10 a.m. - 2 p.m.

- wear long-sleeved shirts, pants, hats and sunglasses

- children under 6 months of age: Ask a doctor

Other information

- protect the product in this container from excessive heat and direct sun

Inactive ingredients

dimethicone, C12-15 alkyl benzoate, dicaprylyl ether, dimethicone/vinyl dimethicone crosspolymer, talc, triethylhexanoin, isohexadecane, styrene/acrylates copolymer, hydrogenated jojoba oil, aluminum hydroxide, stearic acid, aluminum stearate, iron oxides, silica silylate, alumina, polyhydroxystearic acid, PEG-8 lasurate, tocopherol, water, diethylhexyl syringylidenemalonate, laureth-4, disodium stearoyl glutamate, cassia alata leaf extract, maltodextrin, caprylic/capric triglyceride

Questions or comments?

1-888-LRP-LABO 1-888-577-5226

Monday - Friday (9 a.m. - 5 p.m. EST)